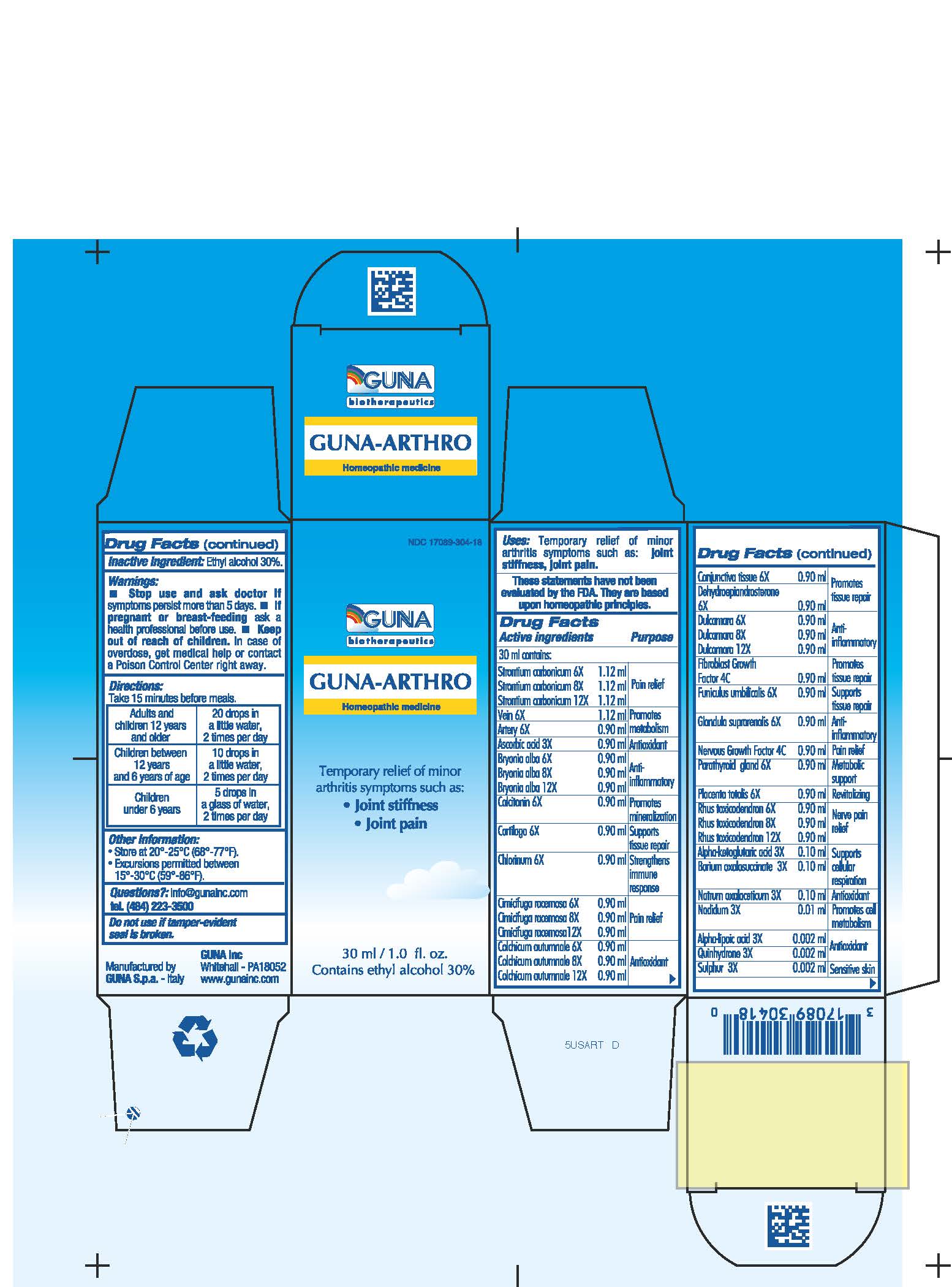 DRUG LABEL: GUNA-ARTHRO
NDC: 17089-304 | Form: SOLUTION/ DROPS
Manufacturer: Guna spa
Category: homeopathic | Type: HUMAN OTC DRUG LABEL
Date: 20221115

ACTIVE INGREDIENTS: SUS SCROFA ARTERY 6 [hp_X]/30 mL; ASCORBIC ACID 3 [hp_X]/30 mL; BARIUM OXALOSUCCINATE 3 [hp_X]/30 mL; BRYONIA ALBA ROOT 6 [hp_X]/30 mL; CALCITONIN HUMAN 6 [hp_X]/30 mL; SUS SCROFA CARTILAGE 6 [hp_X]/30 mL; CHLORINE 6 [hp_X]/30 mL; BLACK COHOSH 6 [hp_X]/30 mL; COLCHICUM AUTUMNALE BULB 6 [hp_X]/30 mL; SUS SCROFA CONJUNCTIVA 6 [hp_X]/30 mL; SOLANUM DULCAMARA FLOWER 6 [hp_X]/30 mL; VELAFERMIN 4 [hp_C]/30 mL; SUS SCROFA UMBILICAL CORD 6 [hp_X]/30 mL; SUS SCROFA ADRENAL GLAND 6 [hp_X]/30 mL; NADIDE 3 [hp_X]/30 mL; SODIUM DIETHYL OXALACETATE 3 [hp_X]/30 mL; NERVE GROWTH FACTOR 4 [hp_C]/30 mL; SUS SCROFA PARATHYROID GLAND 6 [hp_X]/30 mL; SUS SCROFA PLACENTA 6 [hp_X]/30 mL; QUINHYDRONE 3 [hp_X]/30 mL; TOXICODENDRON PUBESCENS LEAF 6 [hp_X]/30 mL; STRONTIUM CARBONATE 6 [hp_X]/30 mL; SULFUR 3 [hp_X]/30 mL; SUS SCROFA VEIN 6 [hp_X]/30 mL; PRASTERONE 6 [hp_X]/30 mL; .ALPHA.-KETOGLUTARIC ACID 3 [hp_X]/30 mL; .ALPHA.-LIPOIC ACID 3 [hp_X]/30 mL
INACTIVE INGREDIENTS: ALCOHOL 9 mL/30 mL

GUNA-ARTHRO

ACTIVE INGREDIENTS/PURPOSE

ALPHA-KETOGLUTARICUM ACID 3X SUPPORTS CELLULAR RESPIRATION
ALPHA-LIPOIC ACID 3X ANTIOXIDANT
ARTERY 6X PROMOTES METABOLISM
ASCORBIC ACID 3X ANTIOXIDANT
BARIUM OXALOSUCCINATE 3X SUPPORTS CELLULAR RESPIRATION
BRYONIA ALBA 6X, 8X, 12X ANTI-INFLAMMATORY
CALCITONIN 6X PROMOTES MINERALIZATION
CARTILAGO 6X SUPPORTS TISSUE REPAIR
CHLORINUM 6X STRENGTHENS IMMUNE RESPONSE
CIMICIFUGA RACEMOSA 6X, 8X, 12X PAIN RELIEF
COLCHICUM AUTUMNALE 6X, 8X, 12X ANTIOXIDANT
CONJUNCTIVA TISSUE 6X PROMOTES TISSUE REPAIR
DEHYDROEPIANDROSTERONE 6X PROMOTES TISSUE REPAIR
DULCAMARA 6X, 8X, 12X ANTI-INFLAMMATORY
FIBROBLAST GROWTH FACTOR 4C PROMOTES TISSUE REPAIR
FUNICULUS UMBILICALIS 6X SUPPORTS TISSUE REPAIR
GLANDULA SUPRARENALIS 6X ANTI-INFLAMMATORY
NADIDUM 3X PROMOTES CELL METABOLISM
NATRUM OXALACETICUM 3X ANTIOXIDANT
NERVOUS GROWTH FACTOR 4C PAIN RELIEF
PARATHYROID GLAND 6X METABOLIC SUPPORT
PLACENTA TOTALIS 6X REVITALIZING
QUINHYDRONE 3X ANTIOXIDANT
RHUS TOXICODENDRON 6X, 8X, 12X NERVE PAIN RELIEF
STRONTIUM CARBONICUM 6X, 8X, 12X PAIN RELIEF
SULPHUR 3X SENSITIVE SKIN
VEIN 6X PROMOTES METABOLISM

USES

Temporary relief of minor arthritis symptoms such as:

- Joint stiffness
- Joint pain

WARNINGS

- Stop use and ask doctor if symptoms persist more than 5 days.
- If pregnant or breast-feeding ask a health professional before use.
- Keep out of reach of children. In case of overdose, get medical help or contact a Poison Control Center right away.
- Contains ethyl alcohol 30%

PREGNANCY

If pregnant or breast-feeding ask a doctor before use

WARNINGS

Keep out of reach of children

DIRECTIONS

Adults and children 12 years and older 20 drops in a little water 2 times per day
Children between 12 years and 6 years of age 10 drops in a little water 2 times per day
Children under 6 years 5 drops in a little water 2 times per day

QUESTIONS

Questions?: info@gunainc.com
Tel. (484) 223-3500

Inactive ingredient: Ethyl alcohol 30%.

INDICATIONS AND USAGE

Take 15 minutes before meals